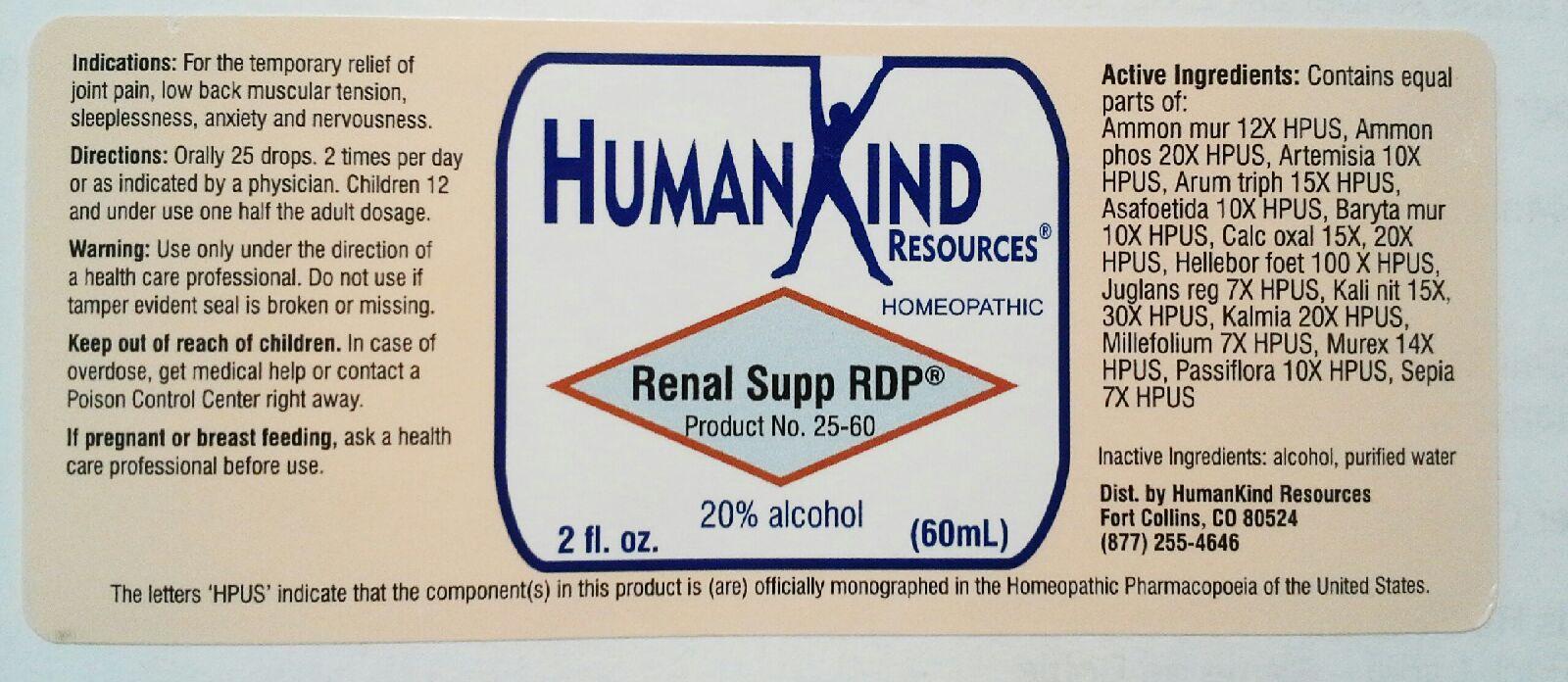 DRUG LABEL: Renal Supp-RDP
NDC: 64616-103 | Form: LIQUID
Manufacturer: Vitality Works, Inc.
Category: homeopathic | Type: HUMAN OTC DRUG LABEL
Date: 20171220

ACTIVE INGREDIENTS: AMMONIUM CHLORIDE 12 [hp_X]/1 mL; AMMONIUM PHOSPHATE, DIBASIC 20 [hp_X]/1 mL; ARTEMISIA VULGARIS ROOT 10 [hp_X]/1 mL; ARISAEMA TRIPHYLLUM ROOT 15 [hp_X]/1 mL; ASAFETIDA 10 [hp_X]/1 mL; BARIUM CHLORIDE DIHYDRATE 10 [hp_X]/1 mL; CALCIUM OXALATE MONOHYDRATE 25 [hp_X]/1 mL; HELLEBORUS FOETIDUS ROOT 100 [hp_X]/1 mL; JUGLANS REGIA LEAF 7 [hp_X]/1 mL; POTASSIUM NITRATE 30 [hp_X]/1 mL; KALMIA LATIFOLIA LEAF 30 [hp_X]/1 mL; ACHILLEA MILLEFOLIUM 7 [hp_X]/1 mL; HEXAPLEX TRUNCULUS HYPOBRANCHIAL GLAND JUICE 14 [hp_X]/1 mL; PASSIFLORA INCARNATA FLOWERING TOP 10 [hp_X]/1 mL; SEPIA OFFICINALIS JUICE 7 [hp_X]/1 mL
INACTIVE INGREDIENTS: ALCOHOL; WATER

Renal Supp-RDP

Renal Supp-RDP

Ammonium Muriaticum 12X Juglans Regia 7X

Ammonium Phosphoricum 20X Kali Nitricum 15X, 30X

Artemisia Vulgaris 10X Kalmia Latifolia 20X

Arum Triphyllum 15X Millefolium 7X

Asafoetida 10X Murex Purpurea 14X

Baryta Muriatica 10 Passiflora Incarnata 10X

Calcarea Oxalica 15X, 25X Sepia 7X

Helleborus Foetidus 100X

Renal Supp-RDP

Alcohol, Purified Water

Renal Supp-RDP

Aids in support and promotion of kidney health.

Renal Supp-RDP

Keep out of reach of children. In case of overdose, get medical help or contact a Poison Control Center right away.

Renal Supp-RDP

For the temporary relief of joint pain, low back muscular tension, sleeplessness, anxiety and nervousness.

Renal Supp-RDP

Orally 25 drops, 2 times per day or as indicated by a physician. Children 12 and under use one half the adult dosage.

Renal Supp-RDP

Desgned to support and promote healing in the kidneys and the entire renal system.